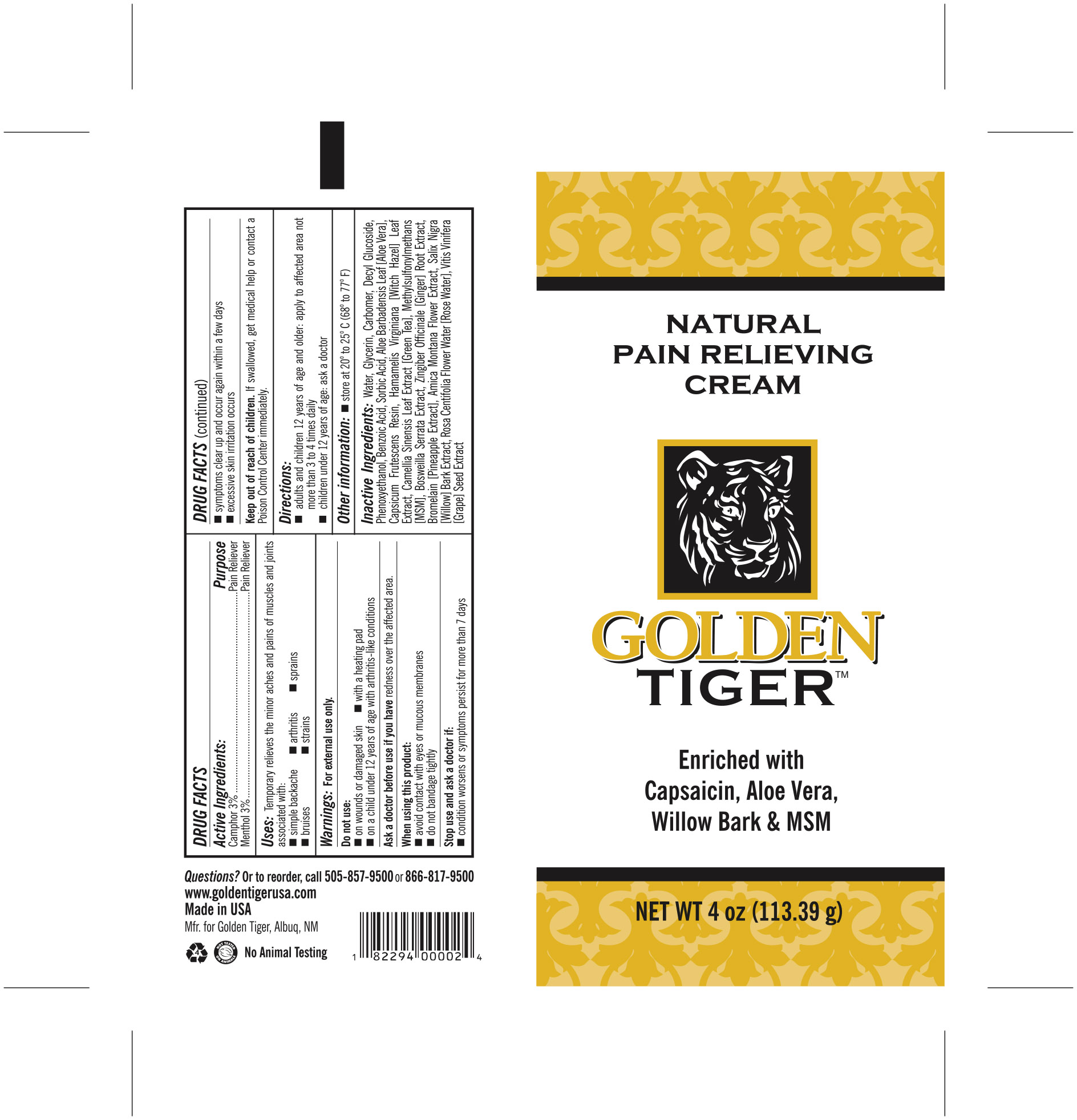 DRUG LABEL: Pain Relieving Cream
NDC: 84334-001 | Form: CREAM
Manufacturer: GOLDEN TIGER DISTRIBUTION L.L.C.
Category: otc | Type: HUMAN OTC DRUG LABEL
Date: 20240712

ACTIVE INGREDIENTS: CAMPHOR (SYNTHETIC) 3 mg/100 mg; MENTHOL 3 mg/100 mg
INACTIVE INGREDIENTS: CARBOMER HOMOPOLYMER, UNSPECIFIED TYPE; CAPSICUM OLEORESIN; INDIAN FRANKINCENSE; BENZOIC ACID; GLYCERIN; ROSA CENTIFOLIA FLOWER OIL; DECYL GLUCOSIDE; GINGER; HAMAMELIS VIRGINIANA TOP; ARNICA MONTANA FLOWER; GREEN TEA LEAF; VITIS VINIFERA SEED; PHENOXYETHANOL; SORBIC ACID; DIMETHYL SULFONE; WATER; BROMELAINS; SALIX NIGRA BARK; ALOE VERA LEAF

Active ingredients

Camphor 3%

Menthol 3%

Purpose

Pain Reliever

Uses

Temporarily relieves the minor aches and pains of muscles and joints associated with:

- simple backache
- arthritis
- sprains
- bruises
- strains

Warnings

For external use only

Do not use

- on wounds or damaged skin
- with a heating pad
- on a child under 12 years of age with arthritis-like conditions

Ask a doctor before use if you have redness over the affected area

When using this product

- avoid contact with eyes or mucous membranes
- do not bandage tightly

Stop use and ask a doctor if

- condition worsens or symptoms persist for more than 7 days
- symptoms clear up and occur again within a few days
- excessive skin irritation occurs

Keep out of reach of children. If swallowed, get medical help or contact a Poison Control Center immediately.

Directions

- adults and children 12 years of age and older: apply to affected area not more than 3 to 4 times daily
- children under 12 years of age: ask a doctor

Other information

- store at 20° to 25° C (68° to 77° F)

Inactive ingredients

Water, Glycerin, Carbomer, Decyl Glucoside, Phenoxyethanol, Benzoic Acid, Sorbic Acid, Aloe Barbadensis Leaf [Aloe Vera], Capsicum Frutescens Resin, Hamamelis Virginiana [Witch Hazel] Leaf Extract, Camellia Sinensis Leaf Extract [Green Tea], Methylsulfonylmethans [MSM], Boswellia Serrata Extract, Zingiber Officinale [Ginger] Root Extract, Bromelain [Pineapple Extract], Arnica Montana Flower Extract, Salix Nigra [Willow] Bark Extract, Rosa Centifolia Flower Water [Rose Water], Vitis Vinifera [Grape] Seed Extract

Questions? Or to reorder, call 505-857-9500 or 866-817-9500

www.goldentigerusa.com

Made in USA

Mfr. for Golden Tiger, Albuq, NM

No Animal Testing

PACKAGE LABEL

GOLDEN TIGER

NATURAL PAIN RELIEVING CREAM

Enriched with Capsaicin, Aloe Vera,

Willow Bark & MSM

NET WT 4 oz (113.39 mg)